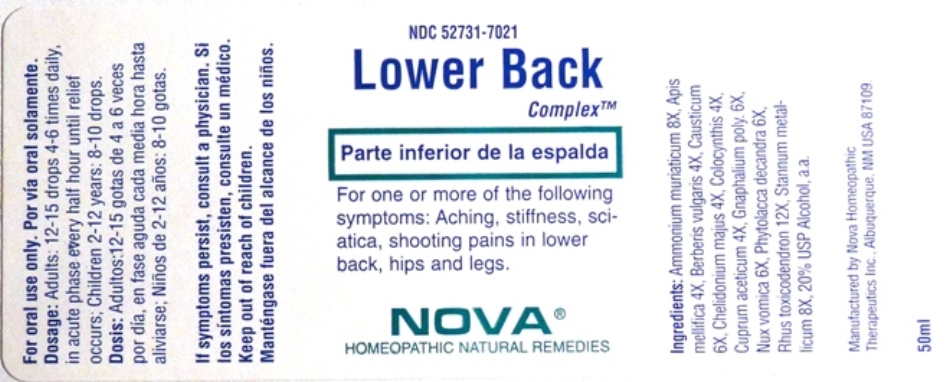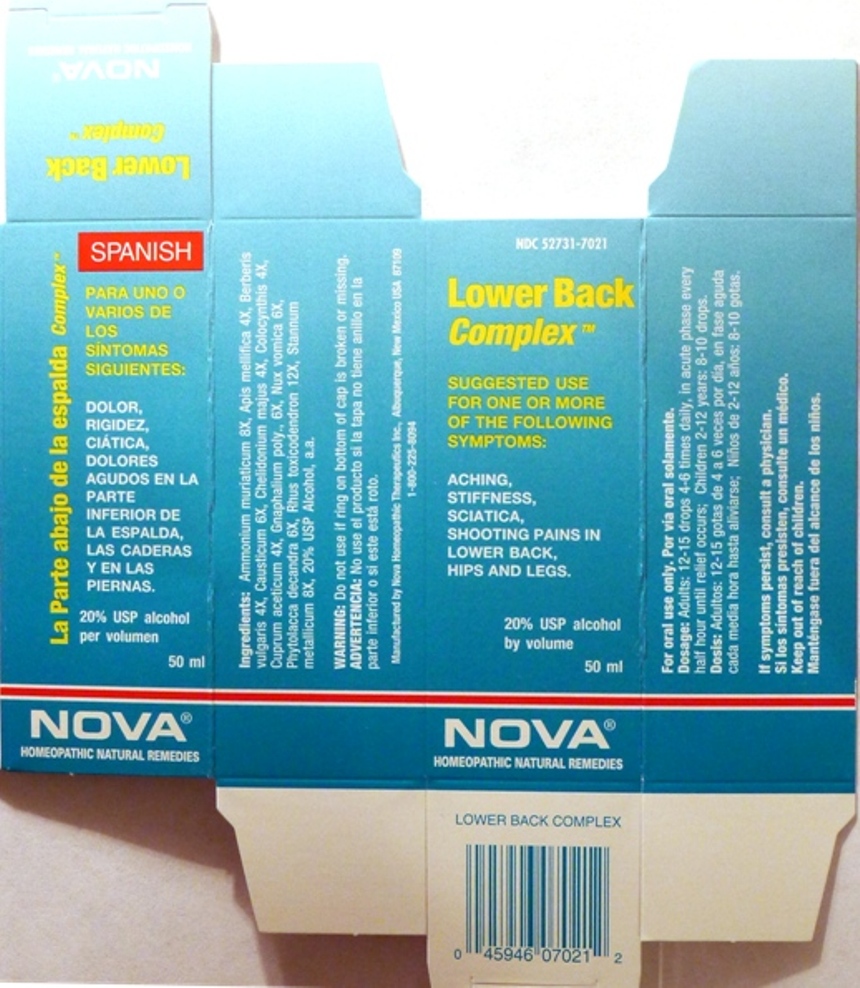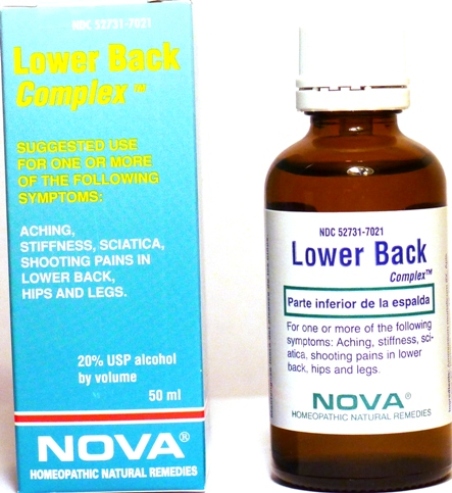 DRUG LABEL: Lower Back Complex
NDC: 52731-7021 | Form: LIQUID
Manufacturer: Nova Homeopathic Therapeutics, Inc.
Category: homeopathic | Type: HUMAN OTC DRUG LABEL
Date: 20110601

ACTIVE INGREDIENTS: AMMONIUM CHLORIDE 8 [hp_X]/1 mL; APIS MELLIFERA 4 [hp_X]/1 mL; BERBERIS VULGARIS ROOT BARK 4 [hp_X]/1 mL; CAUSTICUM 6 [hp_X]/1 mL; CHELIDONIUM MAJUS 4 [hp_X]/1 mL; CITRULLUS COLOCYNTHIS FRUIT PULP 4 [hp_X]/1 mL; CUPRIC ACETATE 4 [hp_X]/1 mL; PSEUDOGNAPHALIUM OBTUSIFOLIUM 6 [hp_X]/1 mL; STRYCHNOS NUX-VOMICA SEED 6 [hp_X]/1 mL; PHYTOLACCA AMERICANA ROOT 6 [hp_X]/1 mL; TOXICODENDRON PUBESCENS LEAF 12 [hp_X]/1 mL; TIN 8 [hp_X]/1 mL
INACTIVE INGREDIENTS: ALCOHOL

Lower Back Complex

Purpose:

Suggested use for one or more of the following symptoms:

Aching,stiffness, sciatica,shooting pains in lower back,hips and legs.

Usage and Dosage:

For oral use only.

DOSAGE AND ADMINISTRATION

Adults:
In Acute Phase:
12-15 drops, every half hour until relief occurs
When Relief Occurs:
12-15 drops, 4-6 times per day
Children 2-12 years:
8-10 drops, 4-6 times per day

Warnings:

Keep out of reach of children.

WARNINGS

If symptoms persist, consult a physician.
Do not use if ring on bottom of cap is broken or missing.

Active Ingredients:

Ammonium muriaticum 8X, Apis mellifica 4X, Berberis vulgaris 4X, Causticum 6X, Chelidonium majus 4X, Colocynthis 4X, Cuprum aceticum 4X, Gnaphalium poly., 6X, Nux vomica 6X, Phytolacca decandra 6X, Rhus toxicodendron 12X, Stannum metallicum 8X

Inactive Ingredients:

Alcohol, 20% USP

QUESTIONS

Manufactured by Nova Homeopathic Therapeutics Inc., Albuquerque, New Mexico USA 87109
1-800-225-8094

PACKAGE LABEL

Lower Back Complex Product

Lower Back Complex Bottle Label

Lower Back Complex Box